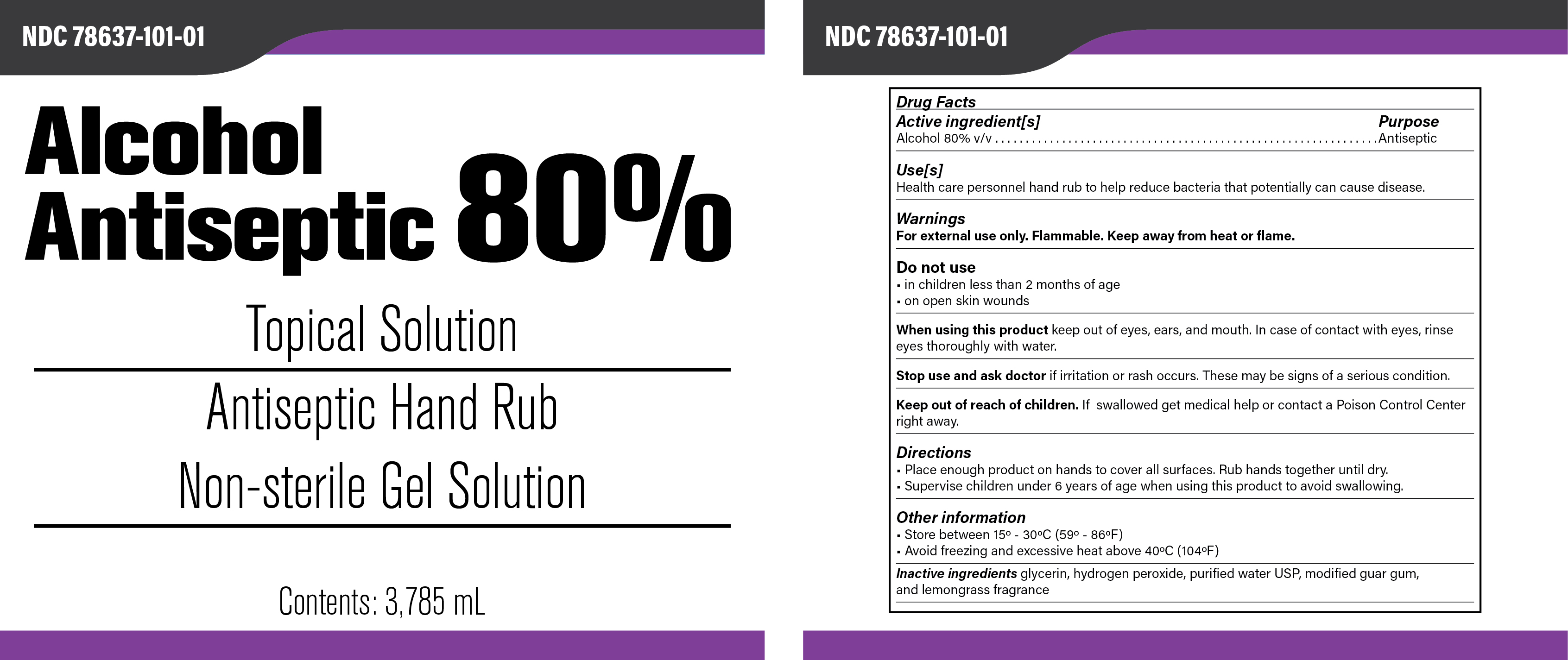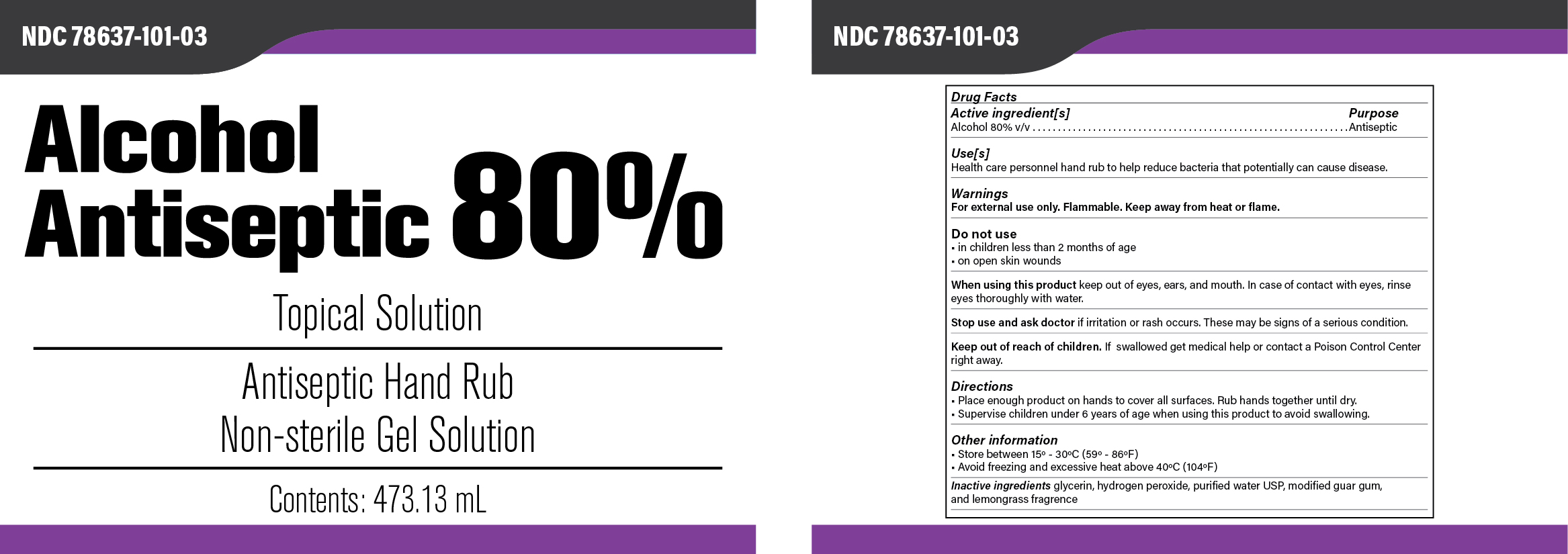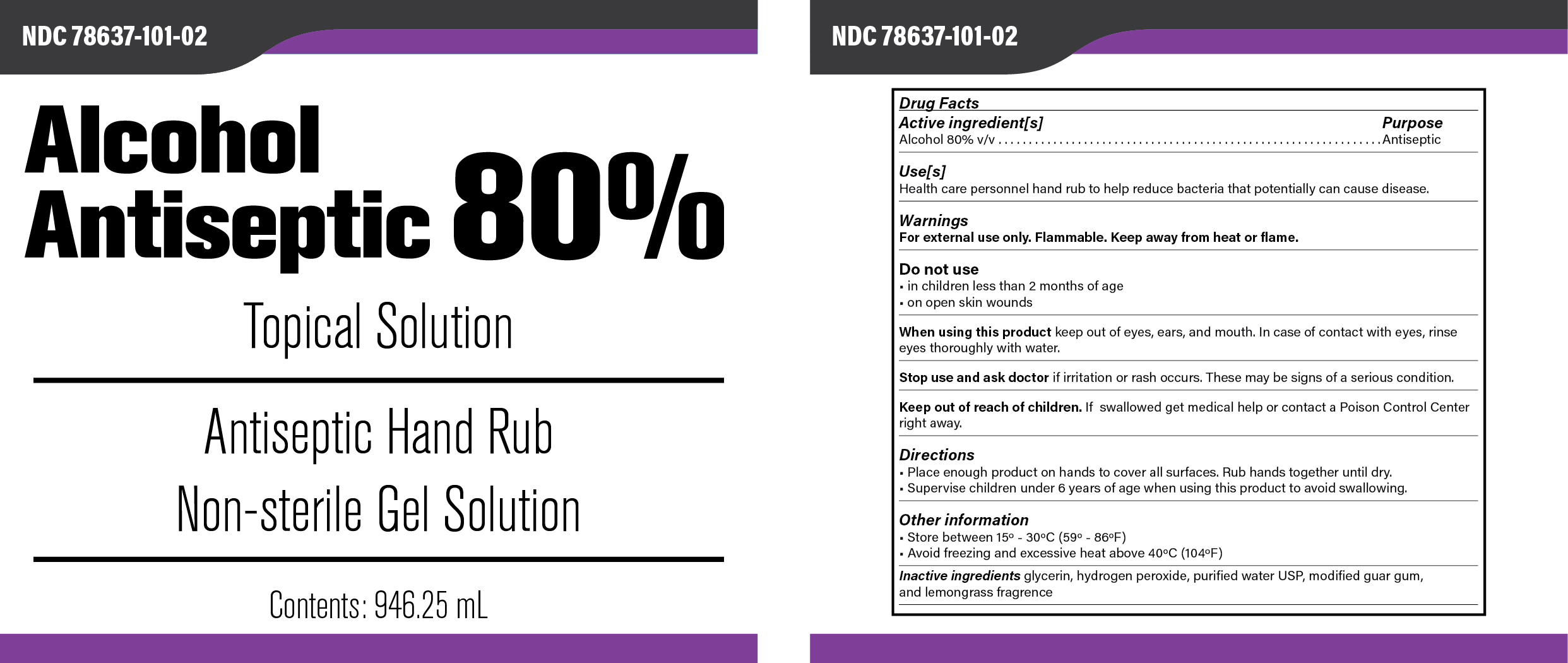 DRUG LABEL: Gel Hand Sanitizer
NDC: 78637-101 | Form: GEL
Manufacturer: Custom Agronomics, Inc.
Category: otc | Type: HUMAN OTC DRUG LABEL
Date: 20200922

ACTIVE INGREDIENTS: ALCOHOL 63.12 g/100 g
INACTIVE INGREDIENTS: LINALYL ACETATE 0.025 g/100 g; .ALPHA.-METHYLBENZYL ACETATE 0.025 g/100 g; 2,6,10-TRIMETHYL-9-UNDECENAL 0.005 g/100 g; 3-(3,4-METHYLENEDIOXYPHENYL)-2-METHYLPROPANAL 0.005 g/100 g; 2-METHYLUNDECANAL 0.005 g/100 g; WEST INDIAN LEMONGRASS OIL 0.35 g/100 g; ORANGE OIL 0.15 g/100 g; 2-ACETONAPHTHONE 0.025 g/100 g; DECANAL 0.005 g/100 g; 2,4-DIMETHYL-3-CYCLOHEXENE CARBOXALDEHYDE 0.025 g/100 g; CYCLAMEN ALDEHYDE 0.005 g/100 g; 1H,5H-CYCLOPENTA(3,4)(1)BENZOPYRANO(6,7,8-IJ)QUINOLIZIN-12(9H)-ONE, 2,3,6,7,10,11-HEXAHYDRO- 0.005 g/100 g; 10-UNDECENAL 0.005 g/100 g; CITRONELLA OIL 0.005 g/100 g; GUARAPROLOSE (1300 MPA.S AT 1%) 0.5 g/100 g; GRAPEFRUIT OIL 0.075 g/100 g; DIPROPYLENE GLYCOL 0.35 g/100 g; GLYCERIN 1.81 g/100 g; HYDROGEN PEROXIDE 0.14 g/100 g; WATER

Gel Hand Sanitizer

This is a hand sanitizer manufactured according to the Temporary Policy for Preparation of Certain Alcohol-Based Hand Sanitizer Products During the Public Health Emergency (CoViD-19); Guidance for Industry.

The hand sanitizer is manufactured using only the following United States Pharmacopoeia (USP) grade ingredients in the preparation of the product (percentage in final product formulation) consistent with World Health Organization (WHO) recommendations:

1. Alcohol (ethanol) (USP or Food Chemical Codex (FCC) grade) (80%, volume/volume (v/v)) in an aqueous solution denatured according to Alcohol and Tobacco Tax and Trade Bureau regulations in 27 CFR part 20.
2. Glycerol (1.45% v/v).
3. Hydrogen peroxide (0.125% v/v).
4. Sterile distilled water or boiled cold water.

The firm does not add other active or inactive ingredients. Different or additional ingredients may impact the quality and potency of the product.

Active Ingredient(s)

Alcohol 80% v/v. Purpose: Antiseptic

Purpose

Antiseptic, Hand Sanitizer

Use

Hand Sanitizer to help reduce bacteria that potentially can cause disease. For use when soap and water are not available.

Warnings

For external use only. Flammable. Keep away from heat or flame

Do not use

- in children less than 2 months of age
- on open skin wounds

When using this product keep out of eyes, ears, and mouth. In case of contact with eyes, rinse eyes thoroughly with water.
Stop use and ask a doctor if irritation or rash occurs. These may be signs of a serious condition.
Keep out of reach of children. If swallowed, get medical help or contact a Poison Control Center right away.

Stop use and ask a doctor if irritation or rash occurs. These may be signs of a serious condition.

Keep out of reach of children. If swallowed, get medical help or contact a Poison Control Center right away.

Directions

- Place enough product on hands to cover all surfaces. Rub hands together until dry.
- Supervise children under 6 years of age when using this product to avoid swallowing.

Other information

- Store between 15-30C (59-86F)
- Avoid freezing and excessive heat above 40C (104F)

Inactive ingredients

glycerin, hydrogen peroxide, purified water USP, modified guar gum, lemongrass fragrance

Package Label - Principal Display Panel

3785 mL NDC: 78637-101-01

946.25 mL NDC: 78637-101-02

473.13 mL NDC: 78637-101-03